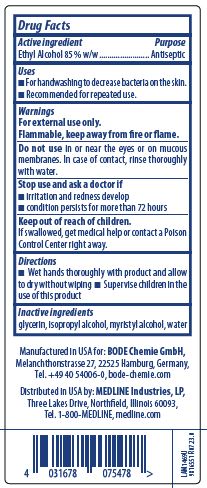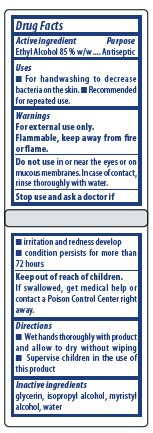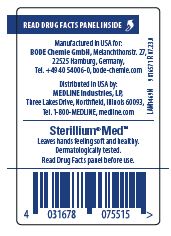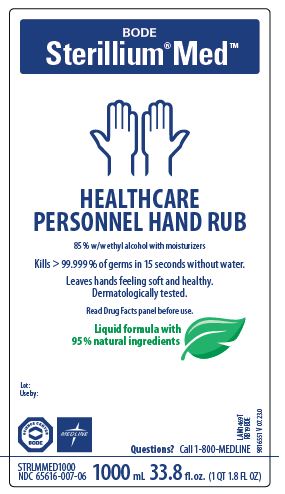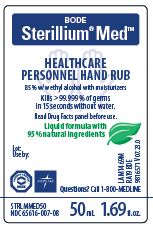 DRUG LABEL: Sterillium Med
NDC: 65616-007 | Form: LIQUID
Manufacturer: BODE Chemie GmbH
Category: otc | Type: HUMAN OTC DRUG LABEL
Date: 20250430

ACTIVE INGREDIENTS: ALCOHOL 89.5 mL/100 mL
INACTIVE INGREDIENTS: GLYCERIN; ISOPROPYL ALCOHOL; WATER; MYRISTYL ALCOHOL

Sterillium Med NDC Number 65616-007

Active ingredient

Ethyl Alcohol 85% w/w

Purpose

Antiseptic

Uses

- For handwashing to decrease bacteria on the skin.
- Recommended for repeated use.

Warnings

For external use only.

Flammable, keep away from fire or flame.

DO NOT USE

Do not usein or near the eyes or on mucous membranes.

In case of contact, rinse thoroughly with water.

Stop use and ask a doctor if

- irritation and redness develop
- condition persists for more than 72 hours

Keep out of reach of children.

If swallowed, get medical help or contact a Poison Control Center right away.

Directions

- Wet hands thoroughly with product and allow to dry without wiping
- Supervise children in the use of this product

Inactive ingredients

Glycerin, Isopropyl Alcohol, Myristyl Alcohol, Water.

Directions

- Wet hands thoroughly with product and allow to dry without wiping
- Supervise children in the use of this product

PACKAGE LABEL

BODE

Sterillium Med

HEALTHCARE

PERSONNEL HAND RUB

85% w/w ethyl alcohol with moisturizers

Kills> 99.999% of germs in 15 seconds without water.

Leaves hands feeling soft and healthy.

Dermatologically Tested.

Read Drug Facts panel before use.

Liquid formula with

95% natural ingredients

Lot:

Use by:

Questions? Call 1-800-MEDLINE

NDC 65615--007-06

1000 mL 33.8 fl. oz.